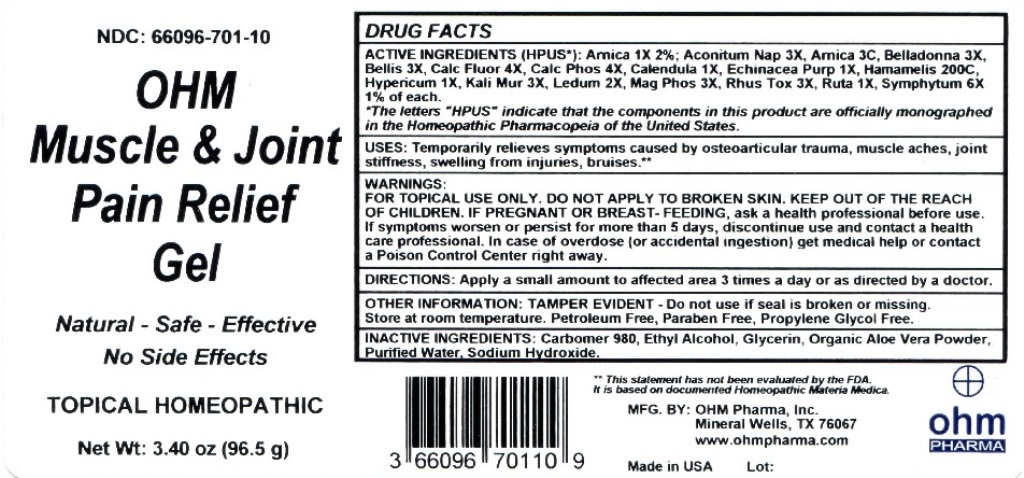 DRUG LABEL: OHM Muscle and Joint Pain Relief Gel
NDC: 66096-701 | Form: GEL
Manufacturer: OHM PHARMA INC.
Category: homeopathic | Type: HUMAN OTC DRUG LABEL
Date: 20211229

ACTIVE INGREDIENTS: ARNICA MONTANA 1 [hp_X]/96.5 g; ACONITUM NAPELLUS 3 [hp_X]/96.5 g; ATROPA BELLADONNA 3 [hp_X]/96.5 g; BELLIS PERENNIS 3 [hp_X]/96.5 g; CALCIUM FLUORIDE 4 [hp_X]/96.5 g; TRIBASIC CALCIUM PHOSPHATE 4 [hp_X]/96.5 g; CALENDULA OFFICINALIS FLOWERING TOP 1 [hp_X]/96.5 g; ECHINACEA PURPUREA 1 [hp_X]/96.5 g; HAMAMELIS VIRGINIANA ROOT BARK/STEM BARK 200 [hp_C]/96.5 g; HYPERICUM PERFORATUM 1 [hp_X]/96.5 g; POTASSIUM CHLORIDE 3 [hp_X]/96.5 g; LEDUM PALUSTRE TWIG 2 [hp_X]/96.5 g; MAGNESIUM PHOSPHATE, DIBASIC TRIHYDRATE 3 [hp_X]/96.5 g; TOXICODENDRON PUBESCENS LEAF 3 [hp_X]/96.5 g; RUTA GRAVEOLENS FLOWERING TOP 1 [hp_X]/96.5 g; COMFREY ROOT 6 [hp_X]/96.5 g
INACTIVE INGREDIENTS: CARBOMER HOMOPOLYMER TYPE C (ALLYL PENTAERYTHRITOL CROSSLINKED); ALCOHOL; GLYCERIN; ALOE VERA LEAF; WATER; SODIUM HYDROXIDE

OHM Muscle & Joint Pain Relief Gel

ACTIVE INGREDIENT

ACTIVE INGREDIENTS (HPUS*): Arnica 1X 2%; Aconitum Nap 3X, Arnica 3C, Belladonna 3X, Bellis 3X, Calc Fluor 4X, Calc Phos 4X, Calendula 1X, Echinacea Purp 1X, Hamamelis 200C, Hypericum 1X, Kali Mur 3X, Ledum 2X, Mag Phos 3X, Rhus Tox 3X, Ruta 1X, Symphytum 6X 1% of each.

*The letters "HPUS" indicate that the components in this product are officially monographed in the Homeopathic Pharmacopeia of the United States.

INDICATIONS AND USAGE

USES: Temporarily relieves symptoms caused by osteoarticular trauma, muscle aches, joint stiffness, swelling from injuries, bruises.**

WARNINGS

WARNINGS: FOR TOPICAL USE ONLY. DO NOT APPLY TO BROKEN SKIN. KEEP OUT OF THE REACH OF CHILDREN. IF PREGNANT OR BREAST - FEEDING, ask a health care professional before use. If symptoms worsen or persist for more than 5 days, discontinue use and contact a health care professional. In case of overdose (or accidental ingestion) get medical help or contact a Poison Control Center right away.

Keep out of the reach of children.

DOSAGE AND ADMINISTRATION

Directions: Apply a small amount to affected area 3 times a day or as directed by a doctor.

OTHER INFORMATION: TAMPER EVIDENT - Do not use if seal is broken or missing. Store at room temperature. Petroleum Free, Paraben Free, Propylene Glycol Free.

**This statement has not been evaluated by the FDA. It is based on documented Homeopathic Materia Medica.

INACTIVE INGREDIENT

INACTIVE INGREDIENTS: Carbomer 980, Ethyl Alcohol, Glycerin, Organic Aloe Vera Powder, Purified Water, Sodium Hydroxide.

QUESTIONS

MFG. By: OHM PHARMA, INC. / Mineral Wells, TX 76067

www.ohmpharma.com

PACKAGE LABEL

NDC: 66096-701-10

OHM

Muscle & Joint

Pain Relief

Gel

Natural - Safe - Effective

No Side Effects

TOPICAL HOMEOPATHIC

Net Wt: 3.40 oz (96.5 g)

PURPOSE

Temporarily relieves symptoms caused by osteoarticular trauma, muscle aches, joint stiffness, swelling from injuries, bruises.